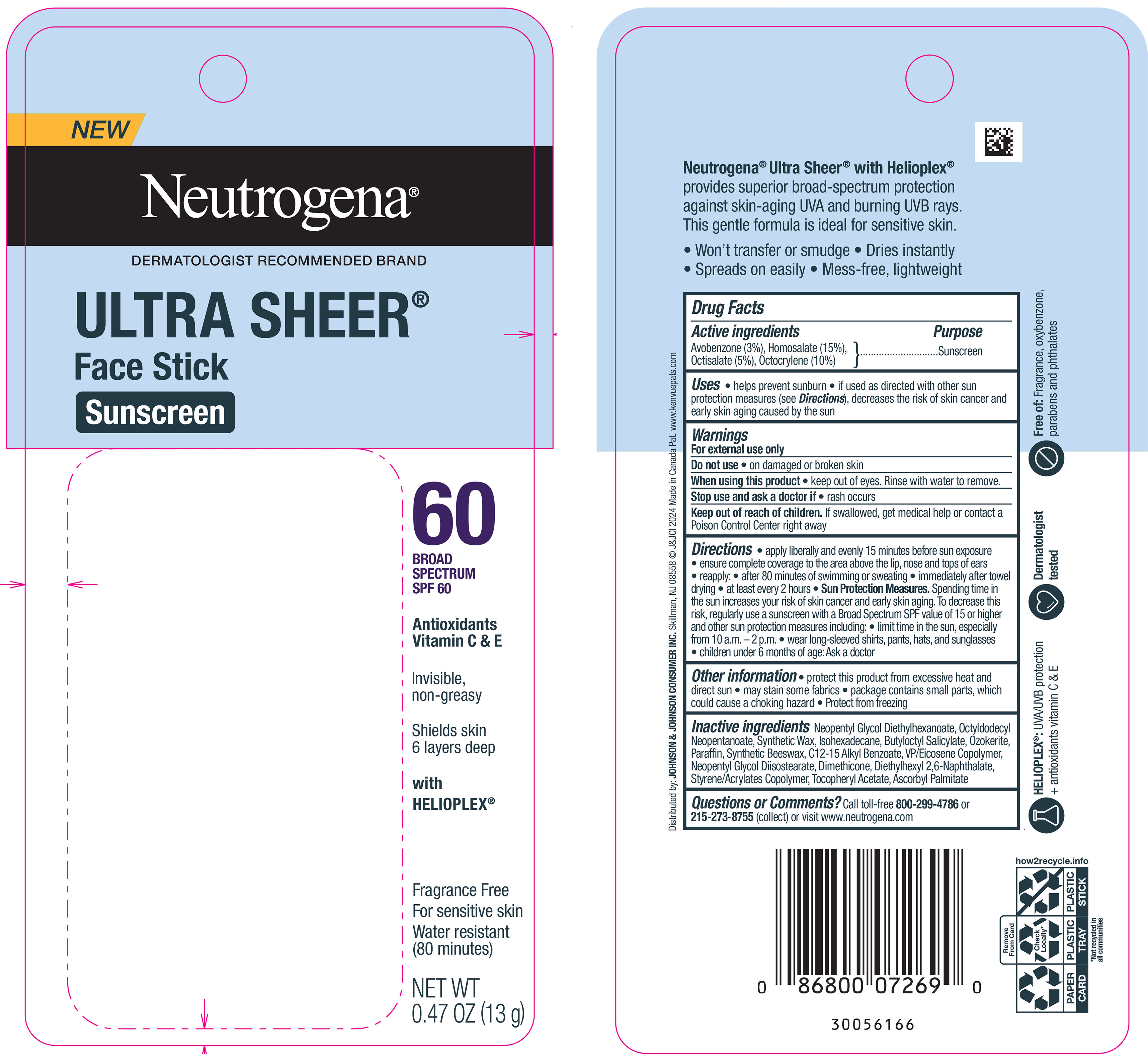 DRUG LABEL: Neutrogena Ultra Sheer Face Sunscreen SPF 60
NDC: 54565-1645 | Form: STICK
Manufacturer: KDC/One Development Corporation, Inc.
Category: otc | Type: HUMAN OTC DRUG LABEL
Date: 20260107

ACTIVE INGREDIENTS: OCTISALATE 50 mg/1 g; OCTOCRYLENE 100 mg/1 g; AVOBENZONE 30 mg/1 g; HOMOSALATE 150 mg/1 g
INACTIVE INGREDIENTS: BUTYLOCTYL SALICYLATE; DIMETHICONE; ASCORBYL PALMITATE; NEOPENTYL GLYCOL DIETHYLHEXANOATE; VINYLPYRROLIDONE/EICOSENE COPOLYMER; CERESIN; SYNTHETIC BEESWAX; OCTYLDODECYL NEOPENTANOATE; PARAFFIN; NEOPENTYL GLYCOL DIISOSTEARATE; ALKYL (C12-15) BENZOATE; ISOHEXADECANE; DIETHYLHEXYL 2,6-NAPHTHALATE; .ALPHA.-TOCOPHEROL ACETATE

Neutrogena Ultra Sheer Face Stick Sunscreen SPF 60

Drug Facts

Active ingredients

Avobenzone (3%),

Homosalate (15%),

Octisalate (5%),

Octocrylene (10%)

Purpose

Sunscreen

Uses

• helps prevent sunburn

• if used as directed with other sun protection measures (see Directions), decreases the risk of skin cancer and early skin aging caused by the sun

Warnings

For external use only

Do not use• on damaged or broken skin

When using this product• keep out of eyes. Rinse with water to remove.

Stop use and ask a doctor if• rash occurs.

Keep out of reach of children.If swallowed, get medical help or contact a Poison Control Center right away.

Directions

• apply liberally and evenly 15 minutes before sun exposure

▪ ensure complete coverage to the area above the lip, nose and tops of ears

▪ reapply:

▪ after 80 minutes of swimming or sweating

▪ immediately after towel drying

▪ at least every 2 hours

▪ Sun Protection Measures.

Spending time in the sun increases your risk of skin cancer and early skin aging. To decrease this risk, regularly use a sunscreen with a Broad Spectrum SPF value of 15 or higher and other sun protection measures including:

▪ limit time in the sun, especially from 10 a.m. – 2 p.m.

▪ wear long-sleeved shirts, pants, hats, and sunglasses

▪ children under 6 months of age: Ask a doctor

Other information

• protect this product from excessive heat and direct sun

• may stain some fabrics

• package contains small parts, which could cause a choking hazard

• Protect from freezing

Inactive ingredients

Neopentyl Glycol Diethylhexanoate, Octyldodecyl Neopentanoate, Synthetic Wax, Isohexadecane, Butyloctyl Salicylate, Ozokerite, Paraffin, Synthetic Beeswax, C12-15 Alkyl Benzoate, VP/Eicosene Copolymer, Neopentyl Glycol Diisostearate, Dimethicone, Diethylhexyl 2,6-Naphthalate, Styrene/Acrylates Copolymer, Tocopheryl Acetate, Ascorbyl Palmitate

Questions or comments?

Call toll-free 800-299-4786or 215-273-8755(collect) or visit www.neutrogena.com

Distributed by:
JOHNSON & JOHNSON
CONSUMER INC.
Skillman, NJ 08558

Neutrogena Ultra Sheer Face Stick Sunscreen SPF 60 - 13 g Canister in Blister Pack Label

New

Neutrogena®

DERMATOLOGIST RECOMMENDED BRAND

ULTRA SHEER®

Face Stick

Sunscreen

60

BROAD

SPECTRUM

SPF 60

Antioxidants

Vitamin C & E

Invisible,

non-greasy

Shields skin

6 layers deep

with

HELIOPLEX®

Fragrance Free

For sensitive skin

Water resistant

(80 minutes)

NET WT

0.47 OZ (13g)